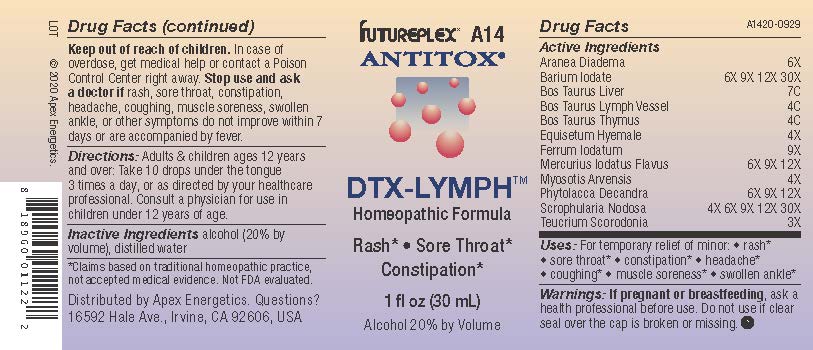 DRUG LABEL: A14
NDC: 63479-0114 | Form: SOLUTION/ DROPS
Manufacturer: Apex Energetics Inc.
Category: homeopathic | Type: HUMAN OTC DRUG LABEL
Date: 20240108

ACTIVE INGREDIENTS: BARIUM IODATE 30 [hp_X]/1 mL; SCROPHULARIA NODOSA 30 [hp_X]/1 mL; TEUCRIUM SCORODONIA FLOWERING TOP 3 [hp_X]/1 mL; ARANEUS DIADEMATUS 6 [hp_X]/1 mL; EQUISETUM HYEMALE 4 [hp_X]/1 mL; FERROUS IODIDE 9 [hp_X]/1 mL; BEEF LIVER 7 [hp_C]/1 mL; BOS TAURUS LYMPH VESSEL 4 [hp_C]/1 mL; MYOSOTIS ARVENSIS 4 [hp_X]/1 mL; PHYTOLACCA AMERICANA ROOT 12 [hp_X]/1 mL; BOS TAURUS THYMUS 4 [hp_C]/1 mL; MERCUROUS IODIDE 12 [hp_X]/1 mL
INACTIVE INGREDIENTS: ALCOHOL; WATER

A14

Active Ingredients
Aranea Diadema | 6X
Barium Iodate | 6X 9X 12X 30X
Bos Taurus Liver | 7C
Bos Taurus Lymph Vessel | 4C
Bos Taurus Thymus | 4C
Equisetum Hyemale | 4X
Ferrum Iodatum | 9X
Mercurius Iodatus Flavus | 6X 9X 12X
Myosotis Arvensis | 4X
Phytolacca Decandra | 6X 9X 12X
Scrophularia Nodosa | 4X 6X 9X 12X 30X
Teucrium Scorodonia | 3X

INDICATIONS AND USAGE

Uses:

For temporary relief of minor:

rash*

sore throat*

constipation*

headache*

coughing*

muscle soreness*

swollen ankle*

*Claims based on traditional homeopathic practice, not accepted medical evidence. Not FDA evaluated.

Warnings:

PREGNANCY OR BREAST FEEDING

If pregnant or breastfeeding, ask a health professional before use.

Do not use if clear seal over the cap is broken or missing.

Keep out of reach of children. In case of overdose, get medical help or contact a Poison Control Center right away.

Stop use and ask a doctor if rash, sore throat, constipation, headache, coughing, muscle soreness, swollen ankle, or other symptoms do not improve within 7 days or are accompanied by fever.

Directions:

Adults & children ages 12 years and over: Take 10 drops under the tongue 3 times a day, or as directed by your healthcare professional. Consult a physician for use in children under 12 years of age.

Inactive Ingredients

alcohol (20% by volume), distilled water

Distributed by Apex Energetics. Questions?

16592 Hale Ave., Irvine, CA 92606, USA

PACKAGE LABEL

FUTUREPLEX® A14

ANTITOX®

DTX-LYMPH™

Homeopathic Formula

Rash*

Sore Throat*

Constipation*

1 fl oz (30 mL)

Alcohol 20% by Volume